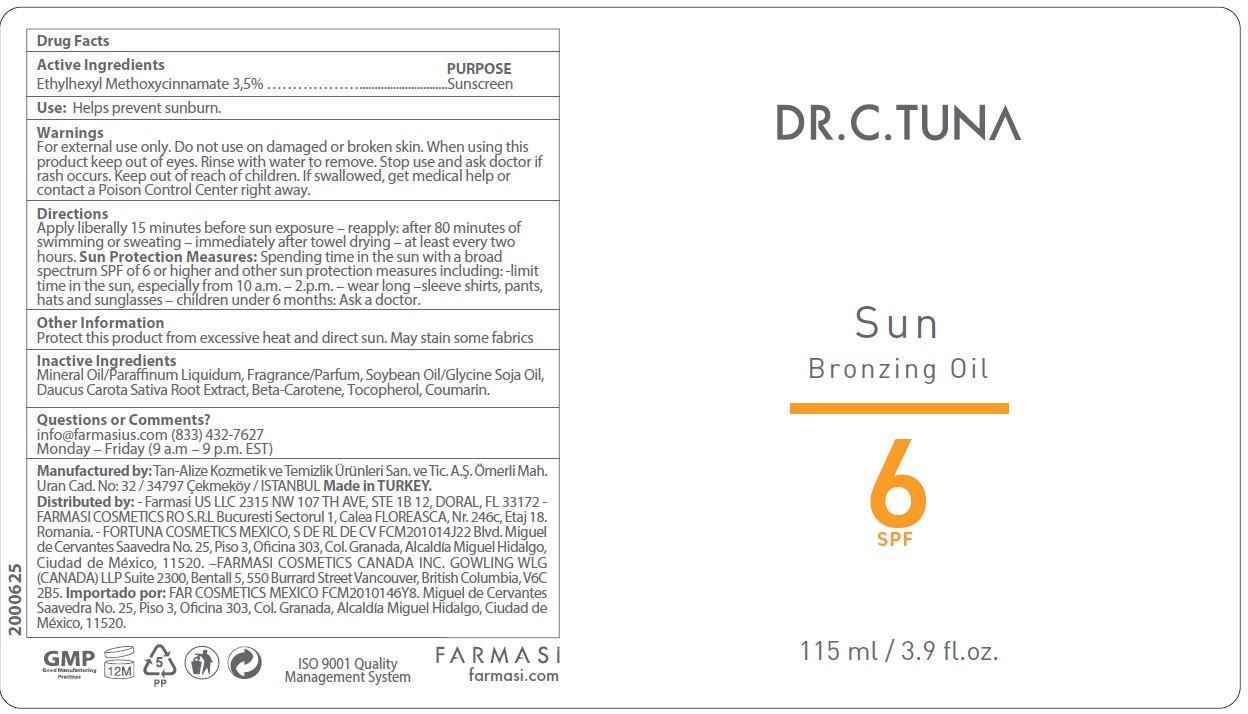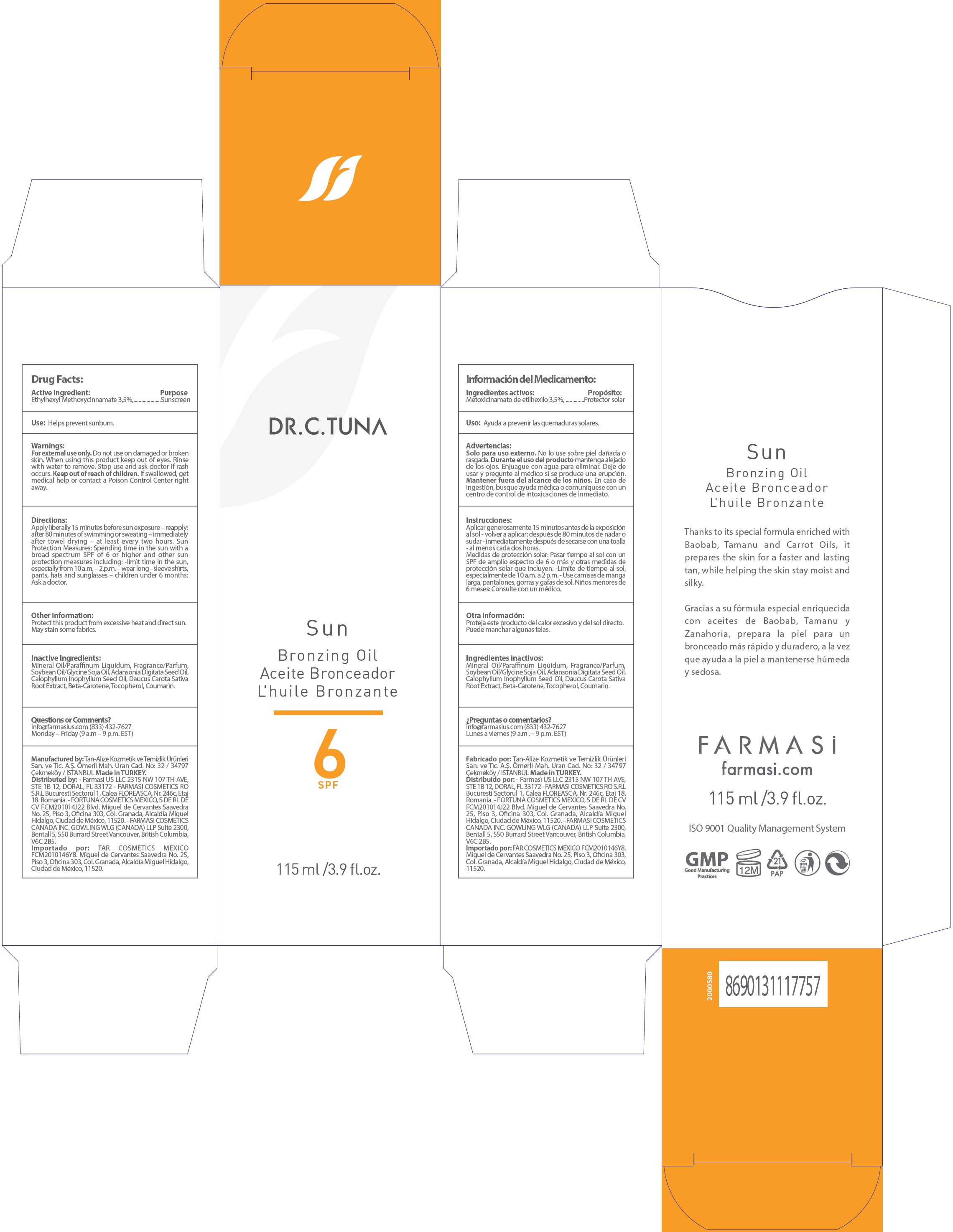 DRUG LABEL: Dr. C. Tuna Sun Bronzing Oil SPF 6
NDC: 74690-014 | Form: OIL
Manufacturer: Farmasi US LLC
Category: otc | Type: HUMAN OTC DRUG LABEL
Date: 20231105

ACTIVE INGREDIENTS: OCTINOXATE 35 mg/1 mL
INACTIVE INGREDIENTS: MINERAL OIL; SOYBEAN OIL; ADANSONIA DIGITATA SEED OIL; TAMANU OIL; CARROT; BETA CAROTENE; TOCOPHEROL; COUMARIN

Dr. C. Tuna Sun Bronzing Oil SPF 6

Active Ingredient:

Ethylhexyl Methoxycinnamate 3,5%

Purpose

Sunscreen

Use:

Helps prevent sunburn.

Warnings:

For external use only.

Do not use

on damaged or broken skin.

When using this product

keep out of eyes. Rinse with water to remove.

Stop use and ask doctor if

rash occurs.

Keep out of reach of children.

If swallowed, get medical help or contact a Poison Control Center right away.

Directions:

Apply liberally 15 minutes before sun exposure – reapply: after 80 minutes of swimming or sweating – immediately after towel drying – at least every two hours. Sun Protection Measures: Spending time in the sun with a broad spectrum SPF of 6 or higher and other sun protection measures including: -limit time in the sun, especially from 10 a.m. – 2.p.m. – wear long –sleeve shirts, pants, hats and sunglasses – children under 6 months: Ask a doctor.

Other Information:

Protect this product from excessive heat and direct sun. May stain some fabrics.

Inactive Ingredients:

Mineral Oil/Paraffinum Liquidum, Fragrance/Parfum, Soybean Oil/Glycine Soja Oil, Adansonia Digitata Seed Oil, Calophyllum Inophyllum Seed Oil, Daucus Carota Sativa Root Extract, Beta-Carotene, Tocopherol, Coumarin.

Questions or Comments?

info@farmasius.com (833) 432-7627

Monday – Friday (9 a.m – 9 p.m. EST)